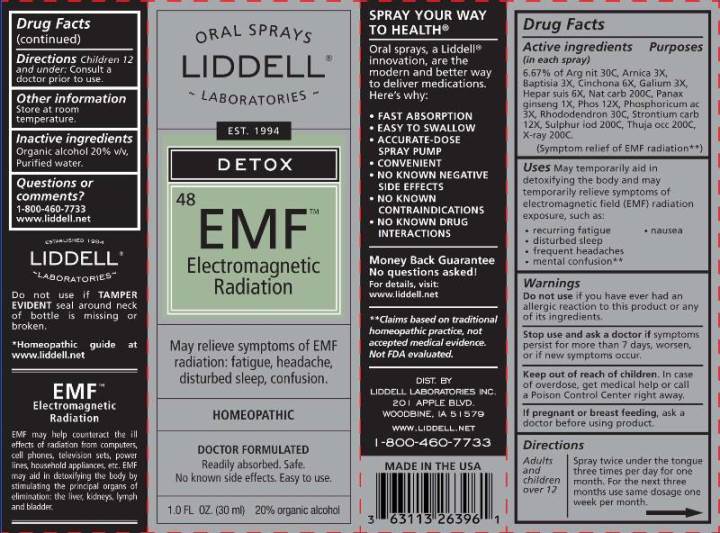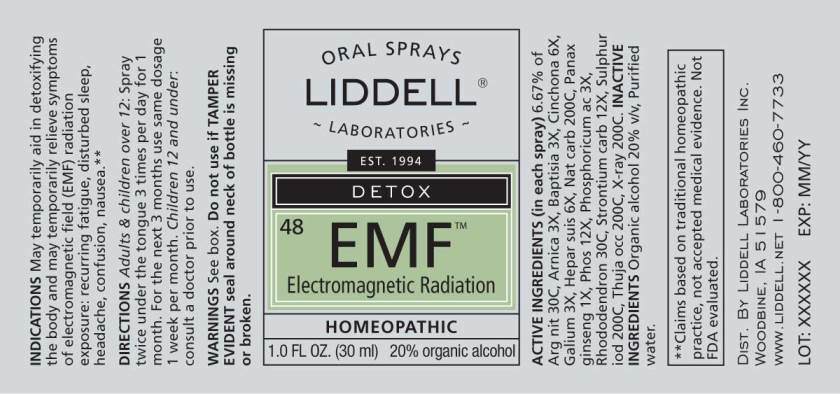 DRUG LABEL: EMF
NDC: 50845-0248 | Form: SPRAY
Manufacturer: Liddell Laboratories, Inc.
Category: homeopathic | Type: HUMAN OTC DRUG LABEL
Date: 20240701

ACTIVE INGREDIENTS: SILVER NITRATE 30 [hp_C]/1 mL; ARNICA MONTANA WHOLE 3 [hp_X]/1 mL; BAPTISIA TINCTORIA ROOT 3 [hp_X]/1 mL; CINCHONA OFFICINALIS BARK 6 [hp_X]/1 mL; GALIUM APARINE WHOLE 3 [hp_X]/1 mL; PORK LIVER 6 [hp_X]/1 mL; SODIUM CARBONATE 200 [hp_C]/1 mL; ASIAN GINSENG 1 [hp_X]/1 mL; PHOSPHORIC ACID 3 [hp_X]/1 mL; PHOSPHORUS 12 [hp_X]/1 mL; RHODODENDRON AUREUM LEAF 30 [hp_C]/1 mL; STRONTIUM CARBONATE 12 [hp_X]/1 mL; SULFUR IODIDE 200 [hp_C]/1 mL; THUJA OCCIDENTALIS LEAFY TWIG 200 [hp_C]/1 mL; ALCOHOL, X-RAY EXPOSED (1000 RAD) 200 [hp_C]/1 mL
INACTIVE INGREDIENTS: WATER; ALCOHOL

DRUG FACTS:

ACTIVE INGREDIENTS:

(in each spray): 6.67% of Argentum nitricum 30C, Arnica montana 3X, Baptisia tinctoria 3X, Cinchona officinalis 6X, Galium aparine 3X, Hepar suis 6X, Natrum carbonicum 200C, Panax ginseng 1X, Phosphorus 12X, Phosphoricum acidum 3X, Rhododendron Chrysanthum 30C, Strontium Carbonicum 12X, Sulphur iodatum 200C, Thuja occidentalis 200C, X-Ray 200C.

USES:

May temporarily aid in detoxifying the body and temporarily relieve symptoms of electromagnetic field (EMF) radiation exposure, such as:

- recurring fatigue
- nausea
- disturbed sleep
- frequent headaches
- mental confusion**

**Claims based on traditional homeopathic practice, not accepted medical evidence. Not FDA evaluated.

WARNINGS:

Do not use if you have ever had an allergic reaction to this product or any of its ingredients.

Stop use and ask a doctor if symptoms persist, worsen or if new symptoms occur.

Keep out of reach of children. In case of overdose, get medical help or call a Poison Control Center right away.

If pregnant or breast feeding, ask a doctor before using product.

Do not use if TAMPER EVIDENT seal around neck of bottle is missing or broken.

Store at room temperature.

Keep out of reach of children. In case of overdose, get medical help or call a Poison Control Center right away.

DIRECTIONS:

Adults and children over 12: Spray twice under the tongue three times per day for one month. For the next three months use same dosage one week per month.

Children 12 and under: Consult a doctor prior to use.

INDICATIONS:

May temporarily aid in detoxifying the body and temporarily relieve symptoms of electromagnetic field (EMF) radiation exposure, such as:

- recurring fatigue
- nausea
- disturbed sleep
- frequent headaches
- mental confusion**

**Claims based on traditional homeopathic practice, not accepted medical evidence. Not FDA evaluated.

INACTIVE INGREDIENTS:

Organic alcohol 20% v/v, Purified water.

QUESTIONS:

DIST. BY

LIDDELL LABORATORIES

201 APPLE BLVD.

WOODBINE, IA 51579

WWW.LIDDELL.NET

1-800-460-7733

PACKAGE LABEL DISPLAY:

ORAL SPRAYS

LIDDELL

LABORATORIES

EST. 1994

DETOX

48 EMF

Electromagnetic

Radiation

May relieve symptoms of EMF
radiation: fatigue, headache,
disturbed sleep, confusion.

HOMEOPATHIC

DOCTOR FORMULATED

Readily absorbed. Safe.

No known side effects. Easy to use.

1.0 FL OZ (30 ml)